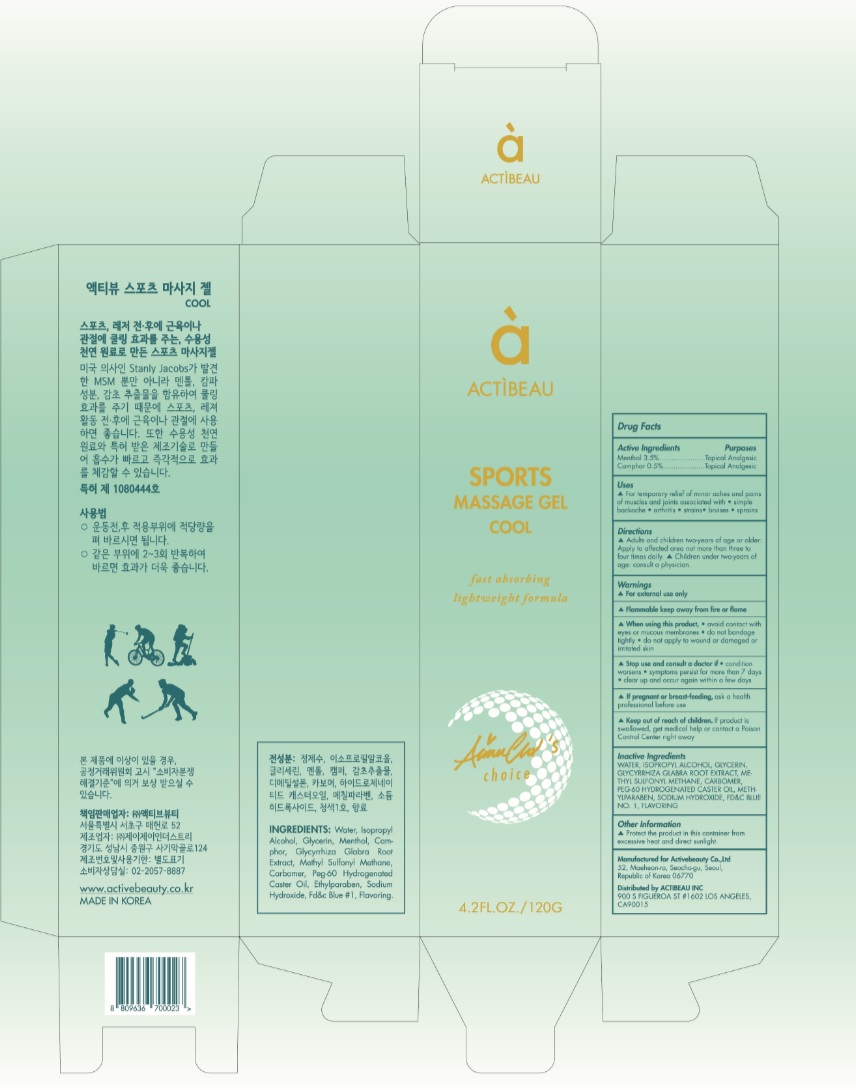 DRUG LABEL: ACTIBEAU Sports Massage
NDC: 73016-002 | Form: GEL
Manufacturer: ACTIVEBEUTY CO.,LTD.
Category: otc | Type: HUMAN OTC DRUG LABEL
Date: 20190401

ACTIVE INGREDIENTS: MENTHOL, UNSPECIFIED FORM 4.2 g/120 g; CAMPHOR (SYNTHETIC) 0.6 g/120 g
INACTIVE INGREDIENTS: WATER; ISOPROPYL ALCOHOL; GLYCERIN; GLYCYRRHIZA GLABRA; DIMETHYL SULFONE; CARBOXYPOLYMETHYLENE; PEG-60 HYDROGENATED CASTOR OIL; METHYLPARABEN; SODIUM HYDROXIDE; FD&C BLUE NO. 1

73016-002

ACTIVE INGREDIENT

Menthol 3.5%

Camphor 0.5%

PURPOSE

Topical Analgesic

INDICATIONS AND USAGE

For temporary relief of minor aches and pains of
muscles and joints associated with • simple backache • arthritis • strains• bruises • sprains

DOSAGE AND ADMINISTRATION

Adults and children two-years of age or older: Apply to affected area not more than three to four times daily, Children under two-years of age: consult a physician.

WARNINGS

For external use only

Flammable keep away from fire or flame

When using this product, • avoid contact with eyes or mucous membranes • do not bandage tightly • do not apply to wound or damaged or irritated skin

Stop use and consult a doctor if • condition worsens • symptoms persist for more than 7 days • clear up and occur again within a few days
If pregnant or breast-feeding, ask a health professional before use

KEEP OUT OF REACH OF CHILDREN

Keep out of reach of the children. If product is swallowed, get medical help or contact a poison control center right away.

INACTIVE INGREDIENT

Water, Isopropyl Alcohol, Glycerin, Glycyrrhiza Glabra Root Extract, Methyl sulfonyl methane, Carbomer, PEG-60 Hydrogenated Caster Oil, Methylparaben, Sodium Hydroxide, FD&C blue No. 1, Flavoring